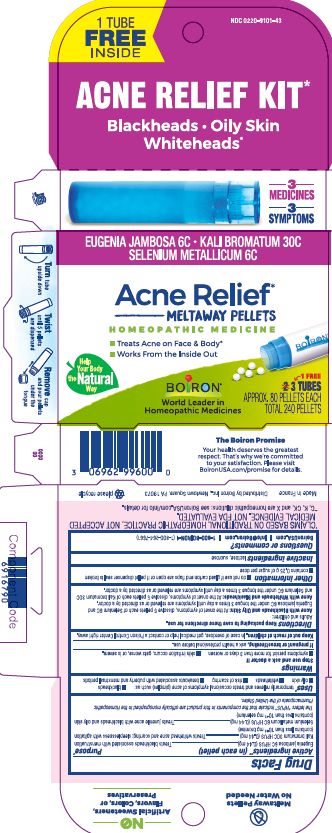 DRUG LABEL: ACNE RELIEF
NDC: 0220-9101 | Form: PELLET
Manufacturer: Boiron
Category: homeopathic | Type: HUMAN OTC DRUG LABEL
Date: 20231004

ACTIVE INGREDIENTS: POTASSIUM BROMIDE 30 [hp_C]/1 1; SYZYGIUM JAMBOS SEED 6 [hp_C]/1 1; SELENIUM 6 [hp_C]/1 1
INACTIVE INGREDIENTS: SUCROSE; LACTOSE, UNSPECIFIED FORM

Acne Relief BCP

Active ingredients** (in each pellet)

Eugenia jambosa 6C HPUS (0.44 mg)

Kali bromatum 30C HPUS (0.44 mg) (contains less than 10^-12 mg bromine)

Selenium metallicum 6C HPUS (0.44 mg) (contains less than 10^-12 mg selenium)

The letters "HPUS" indicate that components in this product are officially monographed in the Homeopathic Pharmacopoeia of the United States.

Purpose*

Eugenia jambosa 6C HPUS (0.44 mg) ... Treats blackheads associated with menstruation

Kali bromatum 30C HPUS (0.44 mg) ... Treats whitehead acne and scarring; sleeplessness with agitation

Selenium metallicum 6C HPUS (0.44 mg) ... Treats juvenile acne with blackheads and oily skin

Uses*

temporarily relieves and treats occasional symptoms of acne (pimples) such as:

- blackheads
- oily skin
- whiteheads
- risk of scarring
- breakouts associated with puberty and menstrual periods

Stop and ask a doctor if

- symptoms persist for more than 3 days or worsen
- skin irritation occurs, gets worse, or is severe.

PREGNANCY OR BREAST FEEDING

If pregnant or breastfeeding, ask a health professional before use.

Keep out of reach of children. In case of overdose, get medical help or contact a Poison Control Center right away.

Directions

Keep packaging to save these directions for use.

Adults and children:

Acne with Blackheads and Oily Skin: At the onset of symptoms, dissolve 5 pellets each of Selenium 6C and Eugenia jambosa 6C under the tongue 3 times a day until symptoms are relieved or as directed by a doctor.

Acne with Whiteheads and Blackheads: At the onset of symptoms, dissolve 5 pellets each of Kali bromatum 30c and Selenium 6C under the tongue 3 times a day until symptoms are relieved or as directed by a doctor.

INACTIVE INGREDIENT

lactose, sucrose

- do not use if glued carton end flaps are open or if pellet dispenser seal is broken
- contains 0.25 g of sugar per dose

ACNE RELIEF KIT*

Blackheads Oily Skin Whiteheads*

Treats Acne on Face & Body*

Works From the Inside Out

3 TUBES

APPROX. 80 PELLETS EACH

TOTAL 240 PELLETS

Turn tube upside down Twist until 5 pellets are dispensed Remove cap and pour pellets under the tongue

*CLAIMS BASED ON TRADITIONAL HOMEOPATHIC PRACTICE NOT ACCEPTED MEDICAL EVIDENCE. NOT FDA EVALUATED.
**C,K,CK, and X are homeopathic dilutions: see BoironUSA.com/info for details.

QUESTIONS

BoironUSA.com

Info@Boiron.com

1-800-BOIRON-1 (1-800-264-7661)

Made in France

Distributed by Boiron, Inc.

Newtown Square, PA 19073